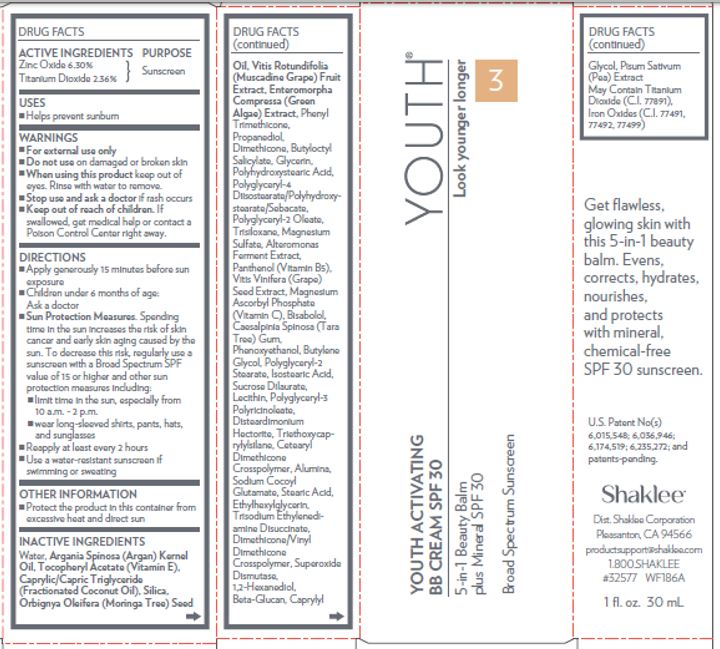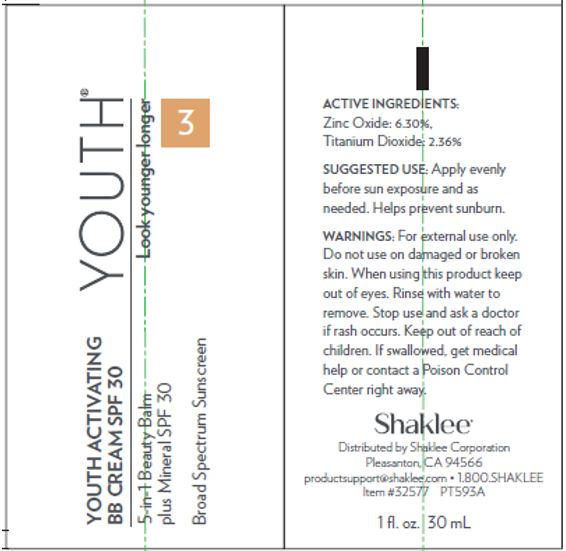 DRUG LABEL: Youth 3 Activating BB Cream SPF 30 Medium
NDC: 59899-012 | Form: LOTION
Manufacturer: Shaklee Corporation
Category: otc | Type: HUMAN OTC DRUG LABEL
Date: 20240606

ACTIVE INGREDIENTS: ZINC OXIDE 63 mg/1 mL; TITANIUM DIOXIDE 23.6 mg/1 mL
INACTIVE INGREDIENTS: BUTYLOCTYL SALICYLATE; GLYCERIN; TRISILOXANE; MAGNESIUM SULFATE, UNSPECIFIED FORM; PANTHENOL; VITIS VINIFERA SEED; MAGNESIUM ASCORBYL PHOSPHATE; LEVOMENOL; CAESALPINIA SPINOSA RESIN; PHENOXYETHANOL; BUTYLENE GLYCOL; POLYGLYCERYL-2 STEARATE; SUCROSE DILAURATE; DISTEARDIMONIUM HECTORITE; TRIETHOXYCAPRYLYLSILANE; ALUMINUM OXIDE; SODIUM COCOYL GLUTAMATE; STEARIC ACID; ETHYLHEXYLGLYCERIN; TRISODIUM ETHYLENEDIAMINE DISUCCINATE; SUPEROXIDE DISMUTASE (SACCHAROMYCES CEREVISIAE); 1,2-HEXANEDIOL; CAPRYLYL GLYCOL; PEA; FERRIC OXIDE YELLOW; FERROSOFERRIC OXIDE; WATER; ARGAN OIL; .ALPHA.-TOCOPHEROL ACETATE; MEDIUM-CHAIN TRIGLYCERIDES; SILICON DIOXIDE; BABASSU OIL; MUSCADINE GRAPE; PROPANEDIOL; DIMETHICONE

Youth 3 Activating BB Cream SPF 30 Medium

ACTIVE INGREDIENT

Zinc Oxide 6.30%

Titanium Dioxide 2.36%

PURPOSE

Sunscreen

USES

- Helps prevent sunburn

WARNINGS

- For external use only

Do not use

on damaged or broken skin

When using this product

keep out of eyes. Rinse with water to remove.

Stop use and ask a doctor

if rash occurs

Keep out of reach of children.

If swallowed, get medical help or contact a Poison Control Center right away.

DIRECTIONS

- Apply generously 15 minutes before sun exposure
- Children under 6 months of age: Ask a doctor
- Spending time in the sun increases the risk of skin cancer and early skin aging caused by the sun. To decrease this risk, regularly use a sunscreen with a Broad Spectrum SPF value of 15 or higher and other sun protection measures including: Sun Protection Measures.
- limit time in the sun, especially from 10 a.m. - 2 p.m.
- wear long-sleeved shirts, pants, hats, and sunglasses
- Reapply at least every 2 hours
- Use a water-resistant sunscreen if swimming or sweating

OTHER INFORMATION

- Protect the product in this container from excessive heat and direct sun

INACTIVE INGREDIENTS

Water, Argania Spinosa (Argan) Kernel Oil, Tocopheryl Acetate (Vitamin E), Caprylic/Capric Triglyceride (Fractionated Coconut Oil), Silica, Orbignya Oleifera (Moringa Tree) Seed Oil, Vitis Rotundifolia (Muscadine Grape) Fruit Extract, Enteromorpha Compressa (Green Algae) Extract, Phenyl Trimethicone, Propanediol, Dimethicone, Butyloctyl Salicylate, Glycerin, Polyhydroxystearic Acid, Polyglyceryl-4 Diisostearate/Polyhydroxystearate/ Sebacate, Polyglyceryl-2 Oleate, Trisiloxane, Magnesium Sulfate, Alteromonas Ferment Extract, Panthenol (Vitamin B5), Vitis Vinifera (Grape) Seed Extract, Magnesium Ascorbyl Phosphate (Vitamin C), Bisabolol, Caesalpinia Spinosa (Tara Tree) Gum, Phenoxyethanol, Butylene Glycol, Polyglyceryl-2 Stearate, Isostearic Acid, Sucrose Dilaurate, Lecithin, Polyglyceryl-3 Polyricinoleate, Disteardimonium Hectorite, Triethoxycaprylylsilane, Cetearyl Dimethicone Crosspolymer, Alumina, Sodium Cocoyl Glutamate, Stearic Acid, Ethylhexylglycerin, Trisodium Ethylenediamine Disuccinate, Dimethicone/Vinyl Dimethicone Crosspolymer, Superoxide Dismutase, 1,2-Hexanediol, Beta-Glucan, Caprylyl Glycol, Pisum Sativum (Pea) Extract May Contain Titanium Dioxide (C.I. 77891), Iron Oxides (C.I. 77491, 77492, 77499)